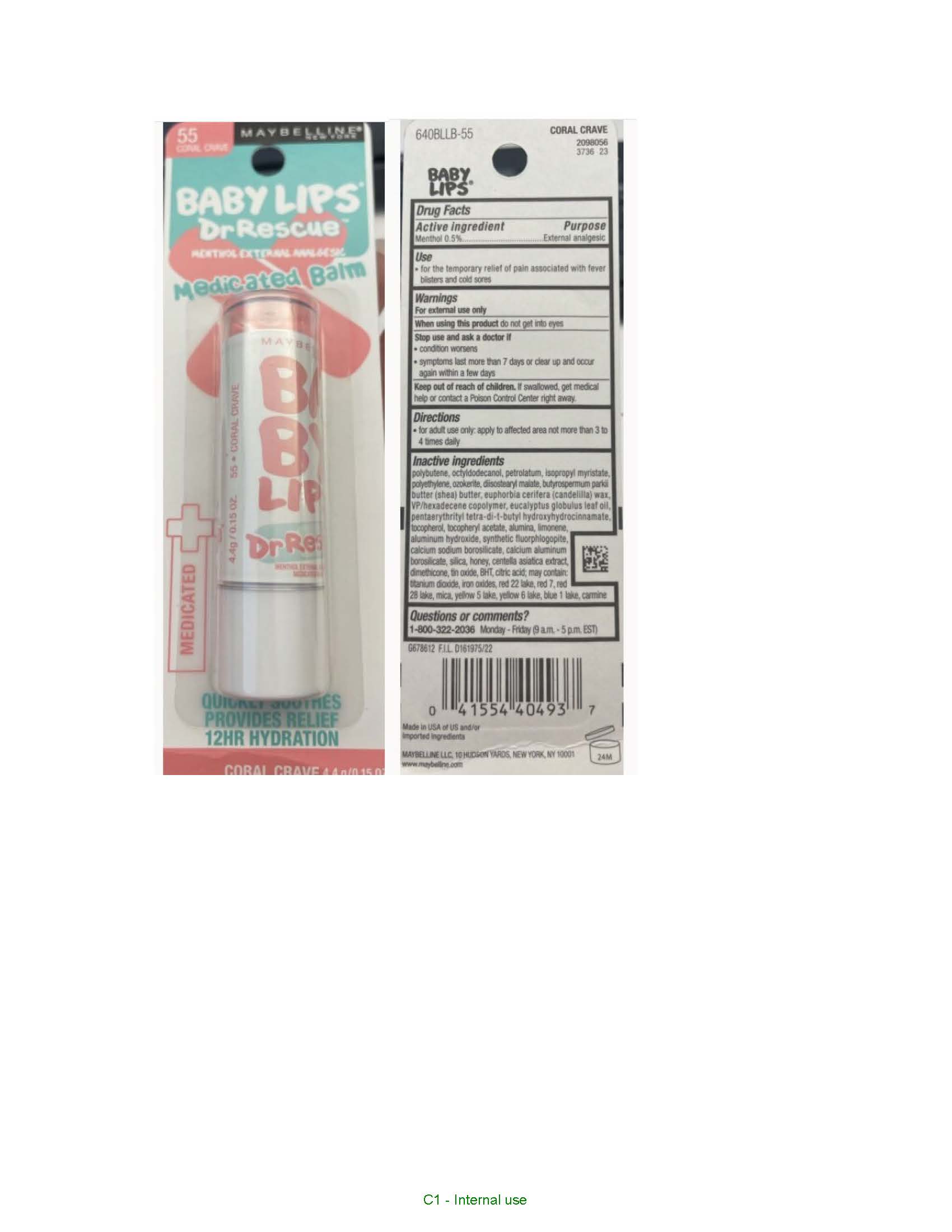 DRUG LABEL: Maybelline New York BABY LIPS DR RESCURE MENTHOL EXTERNAL ANALGESIC MEDICATED BALM
NDC: 49967-494 | Form: LIPSTICK
Manufacturer: L'Oreal USA Products Inc
Category: otc | Type: HUMAN OTC DRUG LABEL
Date: 20240629

ACTIVE INGREDIENTS: MENTHOL 5 mg/1 g
INACTIVE INGREDIENTS: OCTYLDODECANOL; PETROLATUM; ISOPROPYL MYRISTATE; HIGH DENSITY POLYETHYLENE; DIISOSTEARYL MALATE; SHEA BUTTER; CANDELILLA WAX; VINYLPYRROLIDONE/HEXADECENE COPOLYMER; EUCALYPTUS OIL; PENTAERYTHRITOL TETRAKIS(3-(3,5-DI-TERT-BUTYL-4-HYDROXYPHENYL)PROPIONATE); TOCOPHEROL; .ALPHA.-TOCOPHEROL ACETATE; ALUMINUM OXIDE; LIMONENE, (+)-; ALUMINUM HYDROXIDE; CALCIUM SODIUM BOROSILICATE; CALCIUM ALUMINUM BOROSILICATE; SILICON DIOXIDE; HONEY; CENTELLA ASIATICA TRITERPENOIDS; DIMETHICONE; STANNIC OXIDE; BUTYLATED HYDROXYTOLUENE; CITRIC ACID MONOHYDRATE; TITANIUM DIOXIDE; FERRIC OXIDE RED; D&C RED NO. 7; MICA; FD&C YELLOW NO. 6 ALUMINUM LAKE; FD&C BLUE NO. 1 ALUMINUM LAKE

Drug Facts

Active ingredient

Menthol 0.5%

Purpose

External analgesic

Use

- for the temporary relief of pain associated with fever blisters and cold sores

Warnings

For external use only

When using this product

do not get into eyes

Stop use and ask a doctor if

- condition worsens
- symptoms last more than 7 days or clear up and occur again within a few days

Keep out of reach of children.

If swallowed, get medical help or contact a Poison Control Center right away.

Directions

- for adult use only: apply to affected area not more than 3 to 4 times daily

Questions or comments?

1-800-322-2036 Monday - Friday (9 a.m. - 5 p.m. EST)